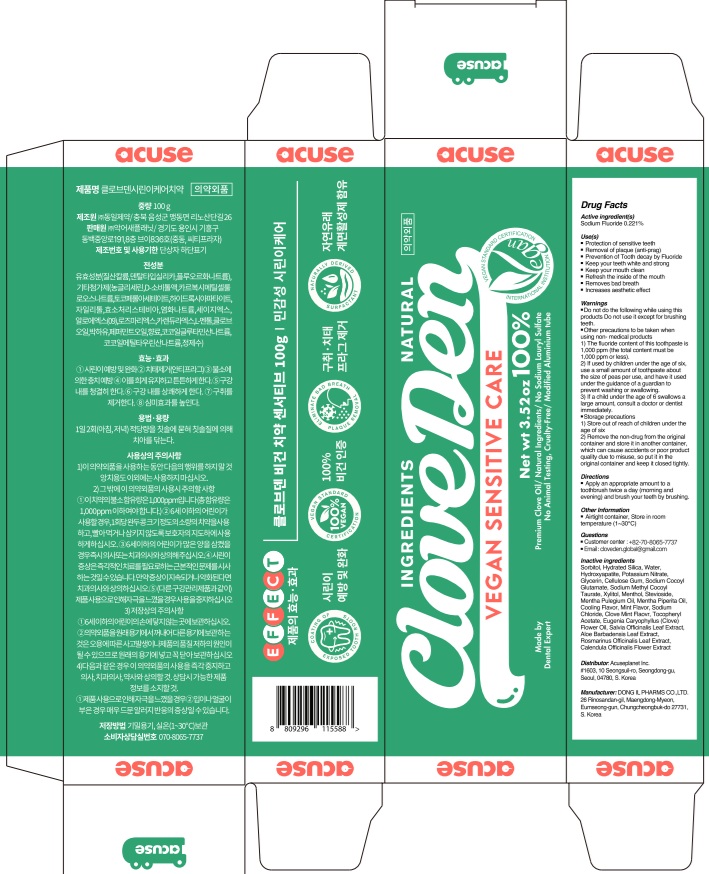 DRUG LABEL: Cloveden Sensitive Care Tooth
NDC: 73242-1113 | Form: PASTE, DENTIFRICE
Manufacturer: DONG IL PHARMS CO.,LTD
Category: otc | Type: HUMAN OTC DRUG LABEL
Date: 20250926

ACTIVE INGREDIENTS: SODIUM FLUORIDE 0.22 g/100 g
INACTIVE INGREDIENTS: TRIBASIC CALCIUM PHOSPHATE; WATER; SORBITOL

Active ingredient(s)

Sodium Fluoride 0.221%

Purpose

Anti-cavity

INDICATIONS AND USAGE

Use(s)

■ Protection of sensitive teeth

■ Removal of plaque (anti-prag)

■ Prevention of Tooth decay by Fluoride

■ Keep your teeth white and strong

■ Keep your mouth clean

■ Refresh the inside of the mouth

■ Removes bad breath

■ Increases aesthetic effect

Warnings

■ Do not do the following while using this products
Do not use it except for brushing teeth.
■ Other precautions to be taken when using non-medical products
1) The fluoride content of this toothpaste is 1,000 ppm (the total content must be 1,000 ppm or less).
2) If used by children under the age of six, use a small amount of toothpaste about the size of peas per use, and have it used under the guidance of a guardian to prevent washing or swallowing.
3) If a child under the age of 6 swallows a large amount, consult a doctor or dentist immediately.
■ Storage precautions
1) Store out of reach of children under the age of six.
2) Remove the non-drug from the original container and store it in another container, which can cause accidents or poor product quality due to misuse, so put it in the original container and keep it closed tightly.

KEEP OUT OF REACH OF CHILDREN

If a child under the age of 6 swallows a large amount, consult a doctor or dentist immediately.

Directions

■ Apply an appropriate amount to a toothbrush twice a day (morning and evening) and brush your teeth by brushing.

Other Information

■ Airtight container, Store in room temperature (1~30℃)

Inactive ingredients

Sorbitol, Hydrated Silica, Water, Hydroxyapatite, Potassium Nitrate, Glycerin, Cellulose Gum, Sodium Cocoyl Glutamate, Sodium Methyl Cocoyl Taurate, Xylitol, Menthol, Stevioside, Mentha Pulegium Oil, Mentha Piperita Oil, Cooling Flavor, Mint Flavor, Sodium Chloride, Clove Mint Flaovr, Tocopheryl Acetate, Eugenia Caryophyllus (Clove) Flower Oil, Salvia Officinalis Leaf Extract, Aloe Barbadensis Leaf Extract, Rosmarinus Officinalis Leaf Extract, Calendula Officinalis Flower Extract